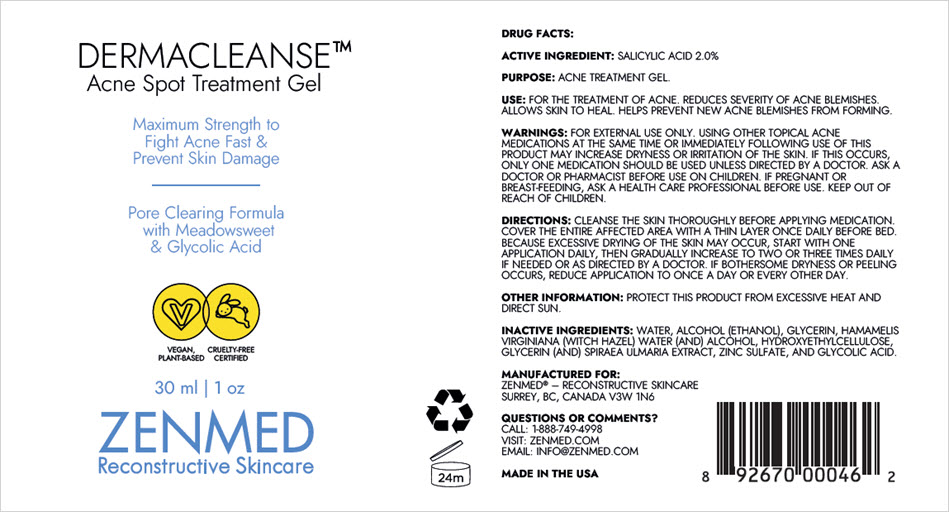 DRUG LABEL: Dermacleanse Acne Spot Treatment
NDC: 83313-0062 | Form: GEL
Manufacturer: ZENMED Raging Creations Ltd.
Category: otc | Type: HUMAN OTC DRUG LABEL
Date: 20251103

ACTIVE INGREDIENTS: SALICYLIC ACID 0.02 g/1 mL
INACTIVE INGREDIENTS: WATER; ALCOHOL; GLYCERIN; HAMAMELIS VIRGINIANA TOP WATER; HYDROXYETHYL CELLULOSE, UNSPECIFIED; FILIPENDULA ULMARIA ROOT; ZINC SULFATE, UNSPECIFIED FORM; GLYCOLIC ACID

DERMACLEANSE™ Acne Spot Treatment Gel

DRUG FACTS:

ACTIVE INGREDIENT

SALICYLIC ACID 2.0%

PURPOSE

ACNE TREATMENT GEL.

USE

FOR THE TREATMENT OF ACNE. REDUCES SEVERITY OF ACNE BLEMISHES. ALLOWS SKIN TO HEAL. HELPS PREVENT NEW ACNE BLEMISHES FROM FORMING.

WARNINGS

FOR EXTERNAL USE ONLY. USING OTHER TOPICAL ACNE MEDICATIONS AT THE SAME TIME OR IMMEDIATELY FOLLOWING USE OF THIS PRODUCT MAY INCREASE DRYNESS OR IRRITATION OF THE SKIN. IF THIS OCCURS, ONLY ONE MEDICATION SHOULD BE USED UNLESS DIRECTED BY A DOCTOR. ASK A DOCTOR OR PHARMACIST BEFORE USE ON CHILDREN. IF PREGNANT OR BREAST-FEEDING, ASK A HEALTH CARE PROFESSIONAL BEFORE USE.

KEEP OUT OF REACH OF CHILDREN.

DIRECTIONS

CLEANSE THE SKIN THOROUGHLY BEFORE APPLYING MEDICATION. COVER THE ENTIRE AFFECTED AREA WITH A THIN LAYER ONCE DAILY BEFORE BED. BECAUSE EXCESSIVE DRYING OF THE SKIN MAY OCCUR, START WITH ONE APPLICATION DAILY, THEN GRADUALLY INCREASE TO TWO OR THREE TIMES DAILY IF NEEDED OR AS DIRECTED BY A DOCTOR. IF BOTHERSOME DRYNESS OR PEELING OCCURS, REDUCE APPLICATION TO ONCE A DAY OR EVERY OTHER DAY.

OTHER INFORMATION

PROTECT THIS PRODUCT FROM EXCESSIVE HEAT AND DIRECT SUN.

INACTIVE INGREDIENTS

WATER, ALCOHOL (ETHANOL), GLYCERIN, HAMAMELIS VIRGINIANA (WITCH HAZEL) WATER (AND) ALCOHOL, HYDROXYETHYLCELLULOSE, GLYCERIN (AND) SPIRAEA ULMARIA EXTRACT, ZINC SULFATE, AND GLYCOLIC ACID.

QUESTIONS OR COMMENTS?

CALL: 1-888-749-4998
VISIT: ZENMED.COM
EMAIL: INFO@ZENMED.COM

PRINCIPAL DISPLAY PANEL - 30 ml Bottle Label

DERMACLEANSE™
Acne Spot Treatment Gel

Maximum Strength to
Fight Acne Fast &
Prevent Skin Damage

Pore Clearing Formula
with Meadowsweet
& Glycolic Acid

VEGAN,
PLANT-BASED

CRUELTY-FREE
CERTIFIED

30 ml | 1 oz

ZENMED
Reconstructive Skincare

24m